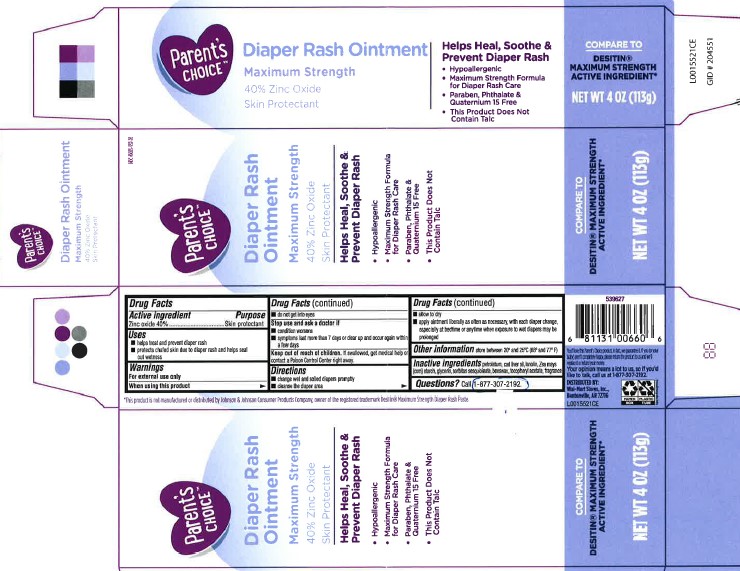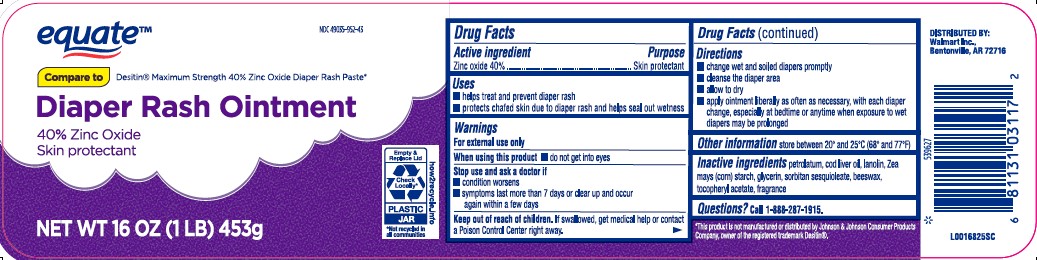 DRUG LABEL: Diaper Rash
NDC: 49035-952 | Form: PASTE
Manufacturer: Walmart Inc.
Category: otc | Type: HUMAN OTC DRUG LABEL
Date: 20260227

ACTIVE INGREDIENTS: ZINC OXIDE 400 mg/1 g
INACTIVE INGREDIENTS: PETROLATUM; COD LIVER OIL; LANOLIN; STARCH, CORN; GLYCERIN; SORBITAN SESQUIOLEATE; YELLOW WAX; .ALPHA.-TOCOPHEROL ACETATE

Equate_Parents Choice 020.002/020AC-AD
Diaper Rash Ointment 40% Zinc Oxide

Active ingredient

Zinc oxide 40%

Purpose

Skin Protectant

Uses

- helps treat and prevent diaper rash
- protects chafed skin due to the diaper rash and helps seal out wetness

Warnings

For external use only

When using this product

- do not get into eyes

Stop use and ask a doctor if

- condition worsens
- symptoms last more than 7 days or clear up and occur again within a few days

Keep out of reach of children.

If swallowed, get medical help or contact a Poison Control Center right away.

Directions

- change wet and soiled diapers promptly
- cleanse the diaper area
- allow to dry
- apply ointment liberally as often as necessary, with each diaper change, especially at bedtime or anytime when exposure to wet diapers may be prolonged

Other information

- store between 20⁰ and 25⁰C (68⁰ and 77⁰F)

Inactive ingredients

petrolatum, cod liver oil, lanolin, Zea mays (corn) starch, glycerin, sorbitan sesquioleate, beeswax, tocopheryl acetate, fragrance

Questions?

Call 1-888-287-1915

Disclaimer

*This product is not manufactured or distributed by Johnson & Johnson Consumer Products Company, owner of the registered trademark Desitin.

ADVERSE REACTION

DISTRIBUTED BY:

Walmart Inc.,

Bentonville, AR 72716

principal display panel

NDC 49035-952-43

equate™

Compare to Desitin®Maximum Strength 40% Zinc Oxide Diaper Rash Paste*

Diaper Rash Ointment

40% ZINC OXIDE

Skin Protectant

Empty & Replace Lid

Check locally*

PLASTIC JAR

*Not recycled in all communities

how2recycle.info

NET WT 16 OZ (1 LB) 453 g

principal display panel

NDC 49035-952-26

Parent's Choice™

Diaper Rash Ointment

Maximum Strength

40% ZINC OXIDE

Skin Protectant

Helps Heal, Soothe & Prevent Diaper Rash

- Hypoallergenic
- Maximum Strength Formula for Diaper Rash Care
- Paraben, Phthalates & Quaternium 15 Free
- This Product Does Not Contain Talc

COMPARE TO DESITIN®MAXIMUM STRENGTH ACTIVE INGREDIENT*

NET WT 4 OZ (113 g)